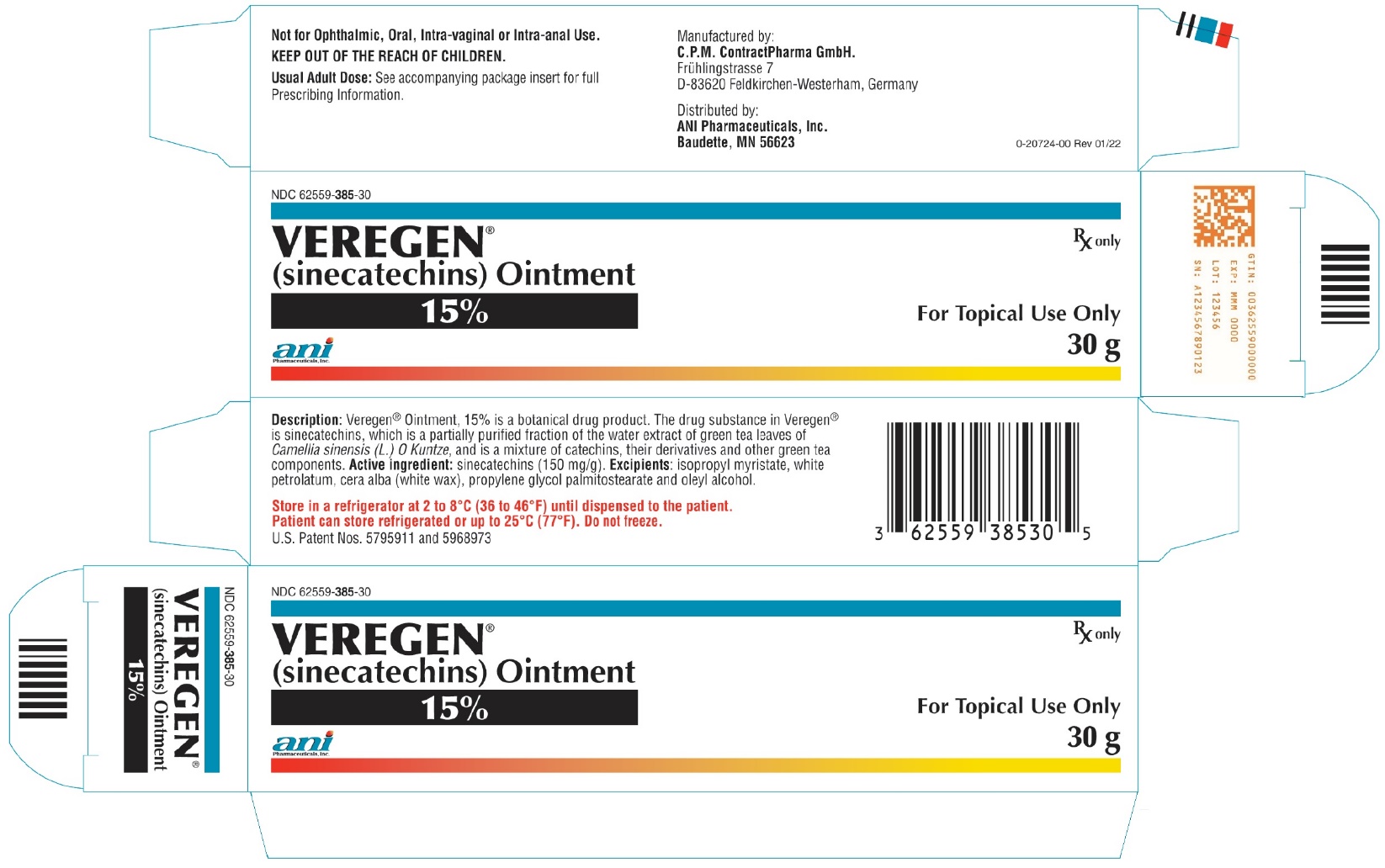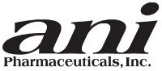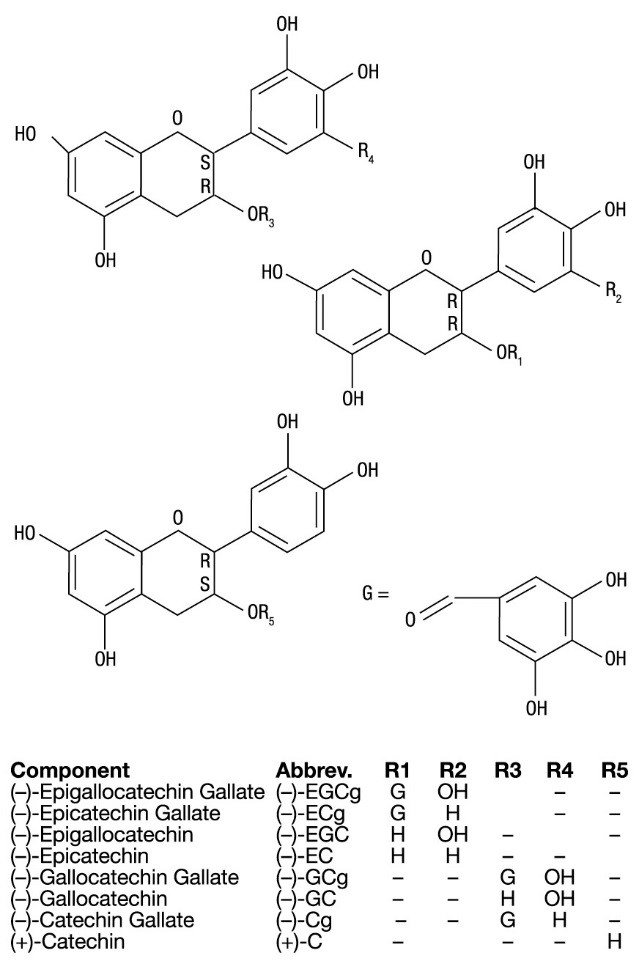 DRUG LABEL: Veregen
NDC: 62559-385 | Form: OINTMENT
Manufacturer: ANI Pharmaceuticals, Inc.
Category: prescription | Type: HUMAN PRESCRIPTION DRUG LABEL
Date: 20221110

ACTIVE INGREDIENTS: SINECATECHINS 150 mg/1 g
INACTIVE INGREDIENTS: ISOPROPYL MYRISTATE; PETROLATUM; WHITE WAX; PROPYLENE GLYCOL MONOPALMITOSTEARATE; OLEYL ALCOHOL

HIGHLIGHTS OF PRESCRIBING INFORMATION

These highlights do not include all the information needed to use VEREGEN safely and effectively. See full prescribing information for VEREGEN.
Veregen® (sinecatechins) ointment, for topical use
Initial U.S. Approval: 2006

1 INDICATIONS AND USAGE

Veregen is a topical ointment indicated for the treatment of external genital and perianal warts (Condylomata acuminata) in immunocompetent patients 18 years and older (1.1).

Limitations of Use
Safety and effectiveness of Veregen have not been established in immunosuppressed patients, in treatment of external genital and perianal warts beyond 16-weeks, or for multiple treatment courses (1.2).

2 DOSAGE AND ADMINISTRATION

- Veregen is to be applied three times per day to all external genital and perianal warts (2.1).
- Apply about an 0.5 cm strand of ointment to each wart using the finger(s), dabbing it on to ensure complete coverage and leaving a thin layer of the ointment on the warts (2.1).
- Veregen is not for ophthalmic, oral, intravaginal, or intra-anal use (2.1).

3 DOSAGE FORMS AND STRENGTHS

Ointment, 15% (3)

4 CONTRAINDICATIONS

None (4)

5 WARNINGS AND PRECAUTIONS

- Veregen should not be used to treat urethral, intra-vaginal, cervical, rectal, or intra-anal human papilloma viral disease (5).
- Use of Veregen on open wounds should be avoided (5).
- Avoid exposure of Veregen treated areas to sun/UV-light as Veregen has not been tested under these circumstances (5).

6 ADVERSE REACTIONS

Most common adverse reactions are local skin and application site reactions including (incidence ≥ 20%) erythema, pruritus, burning, pain/discomfort, erosion/ulceration, edema, induration, and rash vesicular (6).

To report SUSPECTED ADVERSE REACTIONS, ANI Pharmaceuticals, Inc. at 1-800-308-6755 or FDA at 1-800-FDA-1088 or www.fda.gov/medwatch.

FULL PRESCRIBING INFORMATION

1 INDICATIONS AND USAGE

1.1 Indication

Veregen is indicated for the topical treatment of external genital and perianal warts (Condylomata acuminata) in immunocompetent patients 18 years and older.

1.2 Limitations of Use

The safety and effectiveness of Veregen have not been established for treatment beyond 16-weeks or for multiple treatment courses.

The safety and effectiveness of Veregen in immunosuppressed patients have not been established.

2 DOSAGE AND ADMINISTRATION

2.1 General Dosing Information

Veregen is to be applied three times per day to all external genital and perianal warts.

Apply about an 0.5 cm strand of the Veregen to each wart using the finger(s), dabbing it on to ensure complete coverage and leaving a thin layer of the ointment on the warts. Patients should wash their hands before and after application of Veregen.

It is not necessary to wash off the ointment from the treated area prior to the next application.

Veregen® is not for ophthalmic, oral, intravaginal, or intra-anal use.

2.2 Treatment Period

Treatment with Veregen should be continued until complete clearance of all warts, however no longer than 16 weeks.

Local skin reactions (e.g. erythema) at the treatment site are frequent. Nevertheless, treatment should be continued when the severity of the local skin reaction is acceptable.

3 DOSAGE FORMS AND STRENGTHS

Ointment, 15% w/w. Each gram of Veregen Ointment, 15% contains 150 mg of sinecatechins in a brown ointment base.

4 CONTRAINDICATIONS

None

5 WARNINGS AND PRECAUTIONS

Veregen has not been evaluated for the treatment of urethral, intra-vaginal, cervical, rectal, or intra-anal human papilloma viral disease and should not be used for the treatment of these conditions.

Use of Veregen on open wounds should be avoided.

Patients should be advised to avoid exposure of the genital and perianal area to sun/UV-light as Veregen has not been tested under these circumstances.

6 ADVERSE REACTIONS

Because clinical trials are conducted under widely varying conditions, adverse reaction rates observed in the clinical trials of a drug cannot be directly compared to rates in the clinical trials of another drug and may not reflect the rates observed in practice.

In Phase 3 clinical trials, a total of 397 subjects received Veregen three times per day topical application for the treatment of external genital and perianal warts for up to 16 weeks.

Serious local adverse events of pain and inflammation were reported in two subjects (0.5%), both women.

In clinical trials, the incidence of patients with local adverse events leading to discontinuation or dose interruption (reduction) was 5% (19/397). These included the following events: application site reactions (local pain, erythema, vesicles, skin erosion/ulceration), phimosis, inguinal lymphadenitis, urethral meatal stenosis, dysuria, genital herpes simplex, vulvitis, hypersensitivity, pruritus, pyodermitis, skin ulcer, erosions in the urethral meatus, and superinfection of warts and ulcers.

Local and regional reactions (including adenopathy) occurring at >1% in the treated groups are presented in Table 1.

Table 1: Local and Regional Adverse Reactions During Treatment (% Subjects)
 | Veregen® (N = 397) | Vehicle (N = 207)
Erythema | 70 | 32
Pruritus | 69 | 45
Burning | 67 | 31
Pain/discomfort | 56 | 14
Erosion/Ulceration | 49 | 10
Edema | 45 | 11
Induration | 35 | 11
Rash vesicular | 20 | 6
Regional Lymphadenitis | 3 | 1
Desquamation | 5 | <1
Discharge | 3 | <1
Bleeding | 2 | <1
Reaction | 2 | 0
Scar | 1 | 0
Irritation | 1 | 0
Rash | 1 | 0

A total of 266/397 (67%) of subjects in the Veregen group had either a moderate or a severe reaction that was considered probably related to the drug, of which 120 (30%) subjects had a severe reaction. Severe reactions occurred in 37% (71/192) of women and in 24% (49/205) of men. The percentage of subjects with at least one severe, related adverse event was 26% (86/328) for subjects with genital warts only, 42% (19/45) in subjects with both genital and perianal warts and 48% (11/23) of subjects with perianal warts only.

Phimosis occurred in 3% of uncircumcised male subjects (5/174) treated with Veregen and in 1% (1/99) in vehicle.

The maximum mean severity of erythema, erosion, edema, and induration was observed by week 2 of treatment.

Less common local adverse events included urethritis, perianal infection, pigmentation changes, dryness, eczema, hyperesthesia, necrosis, papules, and discoloration. Other less common adverse events included cervical dysplasia, pelvic pain, cutaneous facial rash, and staphylococcemia.

In a dermal sensitization study of Veregen in healthy volunteers, hypersensitivity (type IV) was observed in 5 out of 209 subjects (2.4%) under occlusive conditions.

8 USE IN SPECIFIC POPULATIONS

8.1 Pregnancy

Risk Summary

There are no available data on Veregen use in pregnant women to evaluate for a drug-associated risk of major birth defects, miscarriage, or adverse maternal or fetal outcomes. In animal reproduction studies, sinecatechins did not cause malformations, but did affect the developing fetus in the presence of maternal toxicity when given to pregnant rabbits and rats by intravaginal or systemic routes of administration during the period of organogenesis (see Data). The available data do not allow the calculation of relevant comparisons between the systemic exposure of sinecatechins observed in the animal studies to the systemic exposure that would be expected in humans after topical use of Veregen.

Data

Embryo-fetal development studies were conducted in rats and rabbits using intravaginal and systemic routes of administration, respectively. Oral administration of sinecatechins during the period of organogenesis (gestational Days 6 to 15 in rats or 6 to 18 in rabbits) did not cause treatment-related malformations or effects on embryo-fetal development at doses of up to 1,000 mg/kg/day.

In the presence of maternal toxicity (characterized by marked local irritation at the administration sites and decreased body weight and food consumption) in pregnant female rabbits, subcutaneous doses of 12 and 36 mg/kg/day of sinecatechins during the period of organogenesis (gestational Days 6 to 19) resulted in corresponding influences on fetal development including reduced fetal body weights and delays in skeletal ossification. No treatment-related effects on embryo-fetal development were noted at 4 mg/kg/day. No malformations were noted at any of the doses evaluated in this study.

A combined fertility and embryo-fetal development study using daily vaginal administration of Veregen to rats from Day 4 before mating and throughout mating until Day 17 of gestation did not show treatment-related effects on fertility, malformations, or embryo-fetal development at doses up to 0.15 mL/rat/day. This dose corresponds to approximately 150 mg/rat/day.

A pre- and post-natal development study was conducted in rats using vaginal administration of Veregen at doses of 0.05, 0.10 and 0.15 mL/rat/day from Day 6 of gestation through parturition and lactation. The high and intermediate dose levels of 0.15 and 0.10 mL/rat/day resulted in an increased mortality of the F0 dams, associated with indications of parturition complications. The high dose level of 0.15 mL/rat/day also resulted in an increased incidence of stillbirths. There were no other treatment-related effects on pre- and post-natal development, growth, reproduction and fertility at any dose tested.

8.2 Lactation

Risk Summary

There are no data on the presence of sinecatechins in human or animal milk, the effects on the breastfed child, or the effects on milk production. After topical application, Veregen concentrations in plasma are low and therefore concentrations in human breast milk are likely to be low [see Clinical Pharmacology (12.3)]. The developmental and health benefits of breastfeeding should be considered along with the mother’s clinical need for Veregenand any potential adverse effects on the breast-fed child from Veregenor from the underlying maternal condition.

8.4 Pediatric Use

Safety and effectiveness in pediatric patients have not been established.

8.5 Geriatric Use

Seven patients (1.4%), older than 65 years of age were treated with Veregen in clinical studies. This, however, is an insufficient number of subjects to determine whether they respond differently from younger subjects.

11 DESCRIPTION

Veregen (sinecatechins) Ointment, 15% is a botanical drug product for topical use. The drug substance in Veregen is sinecatechins, which is a partially purified fraction of the water extract of green tea leaves from Camellia sinensis (L.) O Kuntze, and is a mixture of catechins and other green tea components. Catechins constitute 85 to 95% (by weight) of the total drug substance which includes more than 55% of Epigallocatechin gallate (EGCg), other catechin derivatives such as Epicatechin (EC), Epigallocatechin (EGC), Epicatechin gallate (ECg), and some additional minor catechin derivatives i.e. Gallocatechin gallate (GCg), Gallocatechin (GC), Catechin gallate (Cg), and Catechin (C). In addition to the known catechin components, it also contains gallic acid, caffeine, and theobromine which together constitute about 2.5% of the drug substance. The remaining amount of the drug substance contains undefined botanical constituents derived from green tea leaves.

The structural formulae of catechins are shown below.

General Structure of Catechins

Each gram of the ointment contains 150 mg of sinecatechins in a water free ointment base consisting of isopropyl myristate, white petrolatum, cera alba (white wax), propylene glycol palmitostearate, and oleyl alcohol.

12 CLINICAL PHARMACOLOGY

12.1 Mechanism of Action

The mode of action of Veregen involved in the clearance of genital and perianal warts is unknown. In vitro, sinecatechins had anti-oxidative activity; the clinical significance of this finding is unknown.

12.2 Pharmacodynamics

The pharmacodynamics of Veregen is unknown.

12.3 Pharmacokinetics

Systemic exposure to EGCg, EGC, ECg, and EC were evaluated following either topical application of Veregen to subjects with external genital and perianal warts (250 mg applied 3 times a day for 7 days) or following oral ingestion of green tea beverage (500 mL ingested 3 times a day for 7 days). Following topical application of Veregen, plasma concentration of all 4 catechins were below the limit of quantification (<5 ng/mL) on Day 1. After application of Veregen for 7 days, plasma EGC, ECg, and EC concentrations were below the limit of quantification while plasma concentration of EGCg were measurable in 2 out of 20 subjects. The mean maximal plasma concentration (Cmax) of EGCg was 10.1 ng/mL and the mean area under the concentration versus time curve (AUC) of EGCg was 52.2 ng*h/mL in these 2 subjects. Oral ingestion of green tea beverage resulted in measurable concentration of EGCg in all subjects on both Day 1 and Day 7, with mean (SD) Cmax of 23.0 (12.0) ng/mL and AUC of 104.6 (39.0) ng*h/mL on Day 7.

13 NONCLINICAL TOXICOLOGY

13.1 Carcinogenesis, Mutagenesis, Impairment of Fertility

In an oral (gavage) carcinogenicity study, sinecatechins was administered daily for 26 weeks to p53 transgenic mice at doses up to 500 mg/kg/day. Treatment with sinecatechins was not associated with an increased incidence of either neoplastic or non-neoplastic lesions in the organs and tissues examined. Veregen has not been evaluated in a dermal carcinogenicity study.

Sinecatechins was negative in the Ames test, in vivo rat micronucleus assay, UDS test, and transgenic mouse mutation assay, but positive in the mouse lymphoma mutation assay.

Daily vaginal administration of Veregen to rats from Day 4 before mating and throughout mating until Day 17 of gestation did not cause adverse effects on mating performance and fertility at doses up to 0.15 mL/rat/day.

14 CLINICAL STUDIES

Two randomized, double-blind, vehicle-controlled trials were performed to investigate the safety and efficacy of Veregen in the treatment of immunocompetent subjects 18 years of age and older with external genital and perianal warts. The subjects applied the ointment 3 times daily for up to 16 weeks or until complete clearance of all warts (baseline and new warts occurring during treatment).

Over both trials the median baseline wart area was 51 mm^2 (range 12 to 585 mm^2), and the median baseline number of warts was 6 (range 2 to 30).

The primary efficacy outcome measure was the response rate defined as the proportion of subjects with complete clinical (visual) clearance of all external genital and perianal warts (baseline and new) by week 16, presented in Tables 2 and 3 for all randomized subjects dispensed medication.

Table 2: Efficacy by Region
 | Complete Clearance
All Countries (includes the United States)
Veregen® 15% (N = 397) | 213 (53.6%)
Vehicle (N = 207) | 73 (35.3%)
United States
Veregen® 15% (N = 21) | 5 (23.8%)
Vehicle (N = 9) | 0 (0.0%)

Table 3: Efficacy by Gender
 | Complete Clearance
Males
Veregen® 15% (N = 205) | 97 (47.3%)
Vehicle (N = 118) | 34 (28.8%)
Females
Veregen® 15% (N = 192) | 116 (60.4%)
Vehicle (N = 89) | 39 (43.8%)

Median time to complete wart clearance was 16 weeks and 10 weeks, respectively, in the two phase 3 clinical trials.

The rate of recurrence of external genital and perianal warts 12 weeks after completion of treatment in subjects with complete clearance is 6.8% (14/206) for those treated with Veregen and 5.8% (4/69) for those treated with vehicle.

16 HOW SUPPLIED/STORAGE AND HANDLING

Veregen is a brown ointment and is supplied in an aluminum tube containing 30 grams (NDC 62559-385-30) of ointment per tube.

STORAGE AND HANDLING

Prior to dispensing to the patient, store refrigerated 2°C to 8°C (36°F to 46°F). After dispensing, store refrigerated or up to 25°C (77°F). Do not freeze.

KEEP OUT OF THE REACH OF CHILDREN.

17 PATIENT COUNSELING INFORMATION

See FDA-approved patient labeling (Patient Information)

Patients using Veregen should receive the following information and instructions:

- This medication is only to be used as directed by a physician. It is for external use only. Eye contact should be avoided as well as application into the vagina or anus.
- It is not necessary to wash off Veregen prior to the next application. When the treatment area is washed or a bath is taken, the ointment should be applied afterwards.
- It is common for patients to experience local skin reactions such as erythema, erosion, edema, itching, and burning at the site of application. Severe skin reactions can occur and should be promptly reported to the healthcare provider. Should severe local skin reaction occur, the ointment should be removed by washing the treatment area with mild soap and water, and further doses withheld.
- Sexual (genital, anal or oral) contact should be avoided while the ointment is on the skin, or the ointment should be washed off prior to these activities. Veregen may weaken condoms and vaginal diaphragms. Therefore, the use in combination with Veregen is not recommended.
- Female patients using tampons should insert the tampon before applying the ointment. If the tampon is changed while the ointment is on the skin, accidental application of the ointment into the vagina must be avoided.
- Veregen may stain clothing and bedding.
- Veregen is not a cure and new warts might develop during or after a course of therapy. If new warts develop during the 16-week treatment period, these should also be treated with Veregen.
- The effect of Veregen on the transmission of genital/perianal warts is unknown.
- Patients should be advised to avoid exposure of the genital and perianal area to sun/UV light as Veregen has not been tested under these circumstances.
- The treatment area should not be bandaged or otherwise covered or wrapped as to be occlusive.
- Uncircumcised males treating warts under the foreskin should retract the foreskin and clean the area daily.

Patient Package Insert

PATIENT INFORMATION

Veregen®
(sinecatechins)
Ointment, 15%

Read this leaflet carefully before you start using Veregen Ointment and each time you refill your prescription. There may be new information. This information does not take the place of your doctor’s advice. If you have any questions about Veregen Ointment or your condition ask your doctor or pharmacist. Only your doctor can prescribe Veregen and determine if it is right for you.

What is Veregen Ointment?

Veregen Ointment is a medicine for skin use only (topical) for the treatment of warts on the outside of the genitals and around the outside of the anus. It is not a treatment for warts in the vagina, cervix, or inside the anus. Your doctor may recommend examination and screening tests (such as a Pap smear) to evaluate these areas.

Who should not use Veregen Ointment?

Do not use Veregen Ointment if you are allergic to an ingredient in Veregen Ointment. The list of ingredients is at the end of this leaflet.

What should I tell my doctor before using Veregen Ointment?

Tell your doctor about all your health conditions and all the medicines you take including prescription, over-the-counter medicine, vitamins, supplements, and herbals. Be sure to tell your doctor if you are:

- pregnant or planning to become pregnant, as it is not known if Veregen Ointment can harm your unborn baby. Your doctor will determine whether the benefit outweighs the risk.
- breastfeeding, as it is not known if Veregen Ointment can pass into your milk and if it can harm your baby.
- using any other type of skin product or have open wounds on the area to be treated. Veregen Ointment should not be used until your skin has healed from other treatments applied to the same area.
- immunocompromised. This means that your immune system cannot fight infections as well as it should.

How should I use Veregen Ointment?

- Use Veregen Ointment only on the area affected exactly as prescribed by your doctor.
- Wash your hands before and after application of Veregen Ointment. A small amount of the ointment should be applied to all warts using your finger(s), dabbing it on to ensure complete coverage and leaving a thin layer of the ointment on the warts as directed by your doctor.
- Apply Veregen Ointment three times per day — in the morning, at noontime and in the evening. Do not wash off the ointment from the treated area before the next application. When you wash the treatment area or bathe, apply the ointment afterwards.
- Treatment with Veregen Ointment should be continued until complete clearance of all warts, however no longer than 16 weeks. If your warts do not go away, or if they come back after treatment call your doctor.
- Veregen Ointment is not a cure for warts on your genitals or around your anus with certainty. New warts may develop during or after treatment, and may need treatment.

What should I avoid while using Veregen Ointment?

- Do not apply Veregen Ointment on open wounds or into the vagina or into the anus.
- Genital warts are a sexually transmitted disease, and you may infect your partner.
- Avoid sexual contact (genital, anal or oral) when Veregen Ointment is on your genital or perianal skin. If you do choose to have sexual contact, you must wash off the ointment carefully before having protected sexual contact as the ointment may weaken condoms and vaginal diaphragms. Talk to your doctor about safe sex practices.
- Avoid contact with your eyes, nostrils and mouth while ointment is on your finger(s).
- Women using tampons: insert the tampon before applying the ointment. If you need to change your tampon while the ointment is on your skin, avoid getting the ointment into the vagina.
- Uncircumcised men treating warts under the foreskin should retract the foreskin and clean the area daily.
- Do not expose the genital area treated with Veregen Ointment to sunlight, sunlamps or tanning beds.
- Do not cover the treated area. Loose-fitting undergarments can be worn after applying Veregen Ointment.
- Veregen Ointment may stain your light colored clothes and bedding.

What are the possible side effects of Veregen Ointment?

The most common side effects with Veregen Ointment are local skin and application site reactions including:

- redness
- swelling
- sores or blisters
- burning
- itching
- pain

Many patients experience itching, reddening or swelling on or around the application site during the course of treatment. Some of these side effects could be a sign of an allergic reaction. If you experience open sores or other severe reactions at the locations you applied Veregen Ointment, stop treatment and call your doctor right away.

You may experience other side effects of Veregen Ointment which are not mentioned here. Ask your doctor or pharmacist for more information.

Patients should be aware that new warts may develop during treatment as Veregen Ointment is not a cure.

How should I store Veregen Ointment?

- Store Veregen Ointment refrigerated or up to 77°F (25°C).
- Do not freeze.
- Make sure the cap on the tube is tightly closed.
- Safely throw away Veregen Ointment tubes that are out of date or are empty.

Keep Veregen Ointment and all medicines out of the reach of children.

General advice about prescription medicines

Medicines are sometimes prescribed for conditions that are not mentioned in patient information leaflets. Do not use Veregen Ointment for a condition for which it was not prescribed. Do not give Veregen Ointment to other people, even if they have the same symptoms you have. It may harm them.

Do not use Veregen Ointment after the expiration date on the tube.

This leaflet summarizes the most important information about Veregen Ointment. If you would like more information, talk with your doctor. You can ask your pharmacist or doctor for information about Veregen Ointment that is written for the doctor.

For more information, go to www.anipharmaceuticals.com or call 1-800-308-6755.

What are the ingredients in Veregen Ointment?

Active ingredient:

A defined green tea extract named sinecatechins.

Inactive ingredients:

Isopropyl myristate, white petrolatum, cera alba (white wax), propylene glycol palmitostearate, and oleyl alcohol.

Manufactured by:
C.P.M. ContractPharma GmbH.
Frühlingstrasse 7 D-83620
Feldkirchen-Westerham, Germany

Distributed by:
ANI Pharmaceuticals, Inc.
Baudette, MN 56623

U.S. Patent Nos. 5795911 and 5968973

0-20720-00 Rev 01/22

This Patient Information has been approved by the U.S. Food and Drug Administration.

PACKAGE LABEL

VEREGEN®
(sinecatechins) Ointment
15 %
For Topical Use Only
30g